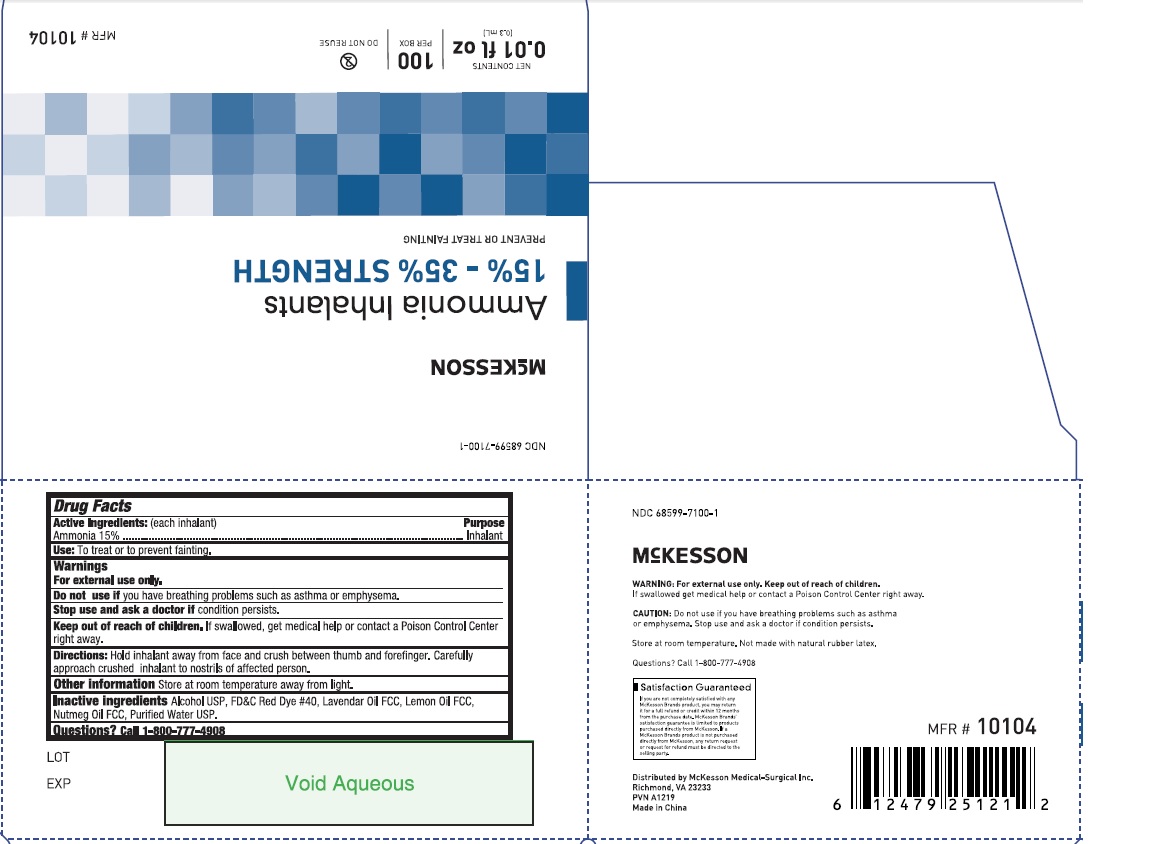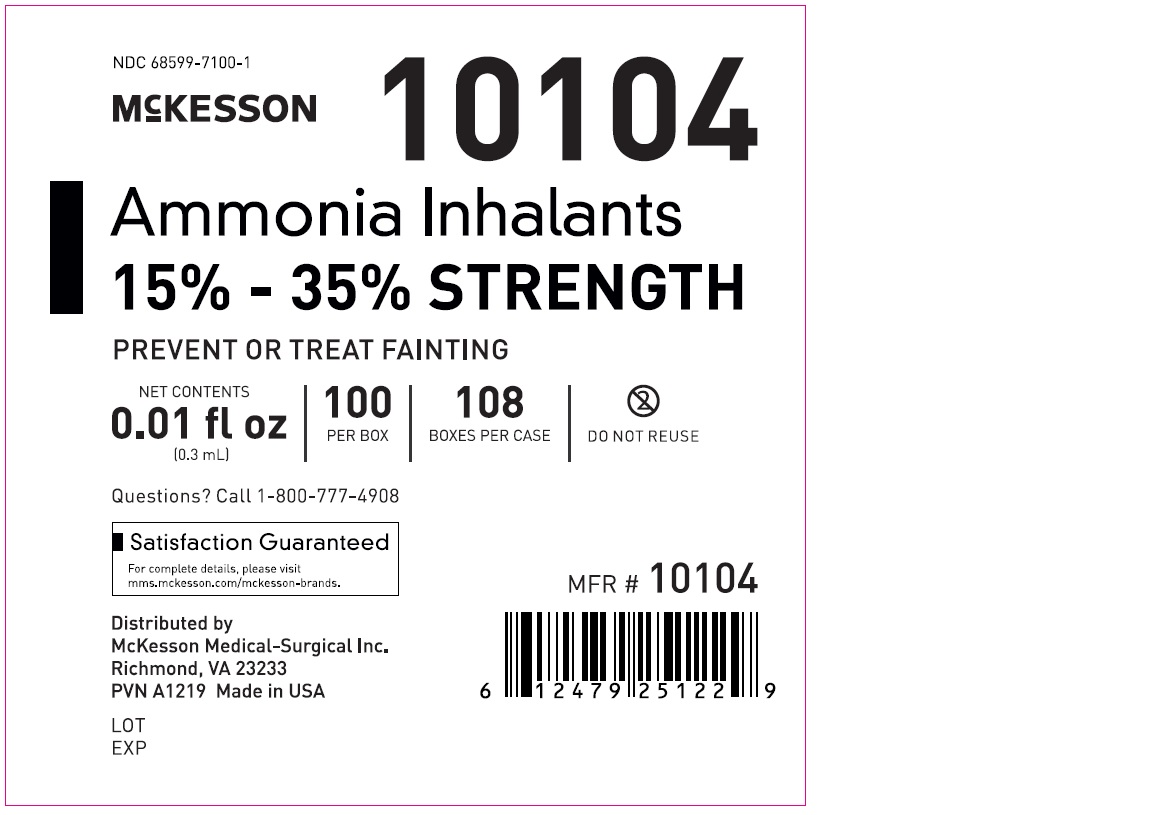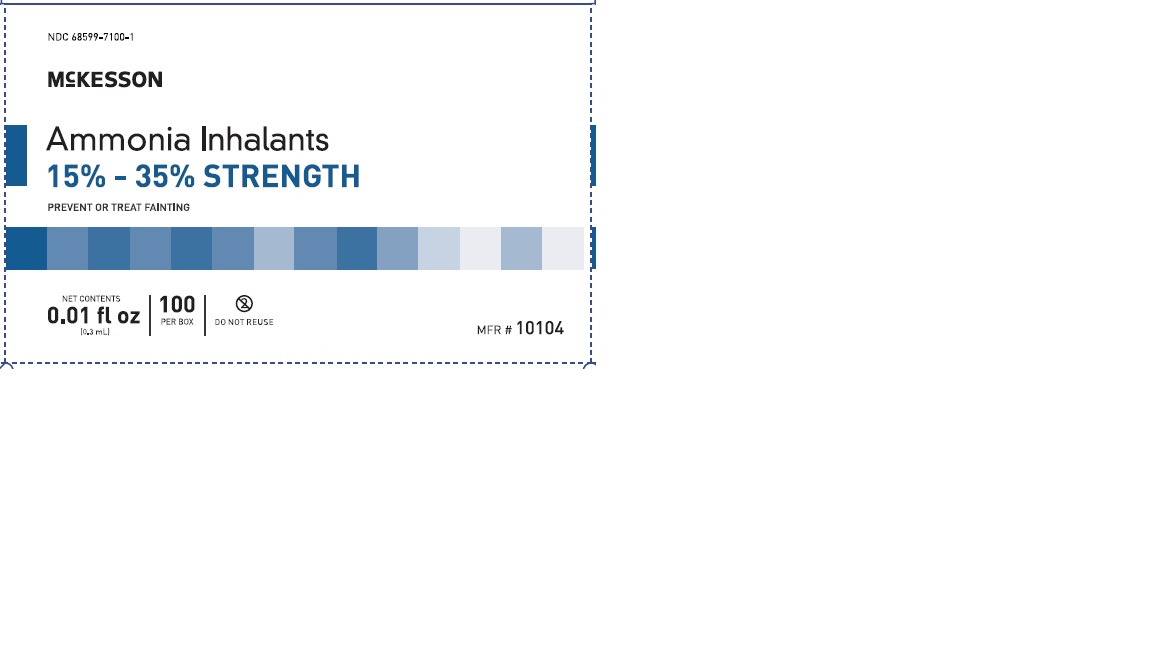 DRUG LABEL: Ammonia
NDC: 68599-7100 | Form: AEROSOL
Manufacturer: McKesson
Category: otc | Type: HUMAN OTC DRUG LABEL
Date: 20210902

ACTIVE INGREDIENTS: AMMONIA 0.15 g/1 g
INACTIVE INGREDIENTS: ALCOHOL; FD&C RED NO. 40; LAVENDER OIL; NUTMEG OIL; WATER; LEMON OIL

Ammonia Inhalant

Active Ingredients (each inhalant)

Ammonia (15%)

Purpose

Inhalant

INDICATIONS AND USAGE

Uses To prevent or treat fainting.

Warnings
For external use only.

Do not use if you have breathing problems such as asthma or emphysema.

Stop use and ask a doctor if condition persists.

Keep out of reach of children. If swallowed get medical help or contact a Poison Control
Center right away.

DOSAGE AND ADMINISTRATION

Directions Hold inhalant away from face and crush between thumb and forefinger. Carefully
approach crushed inhalant to nostrils of affected person.

Other Information Store at room temperature away from light.

INACTIVE INGREDIENT

Inactive Ingredients Alcohol USP, FD&C Red Dye # 40, Lavender Oil FCC, Lemon Oil FCC,
Nutmeg Oil FCC, Purified Water USP.

Questions? Call 1-800-777-4908

PACKAGE LABEL

NDC 68599-7100-1

McKesson
Ammonia Inhalants
15% - 35% Strength
Prevent or Treat Fainting
Net Contents
0.01 fl oz
(0.3 mL)

MFR# 10104